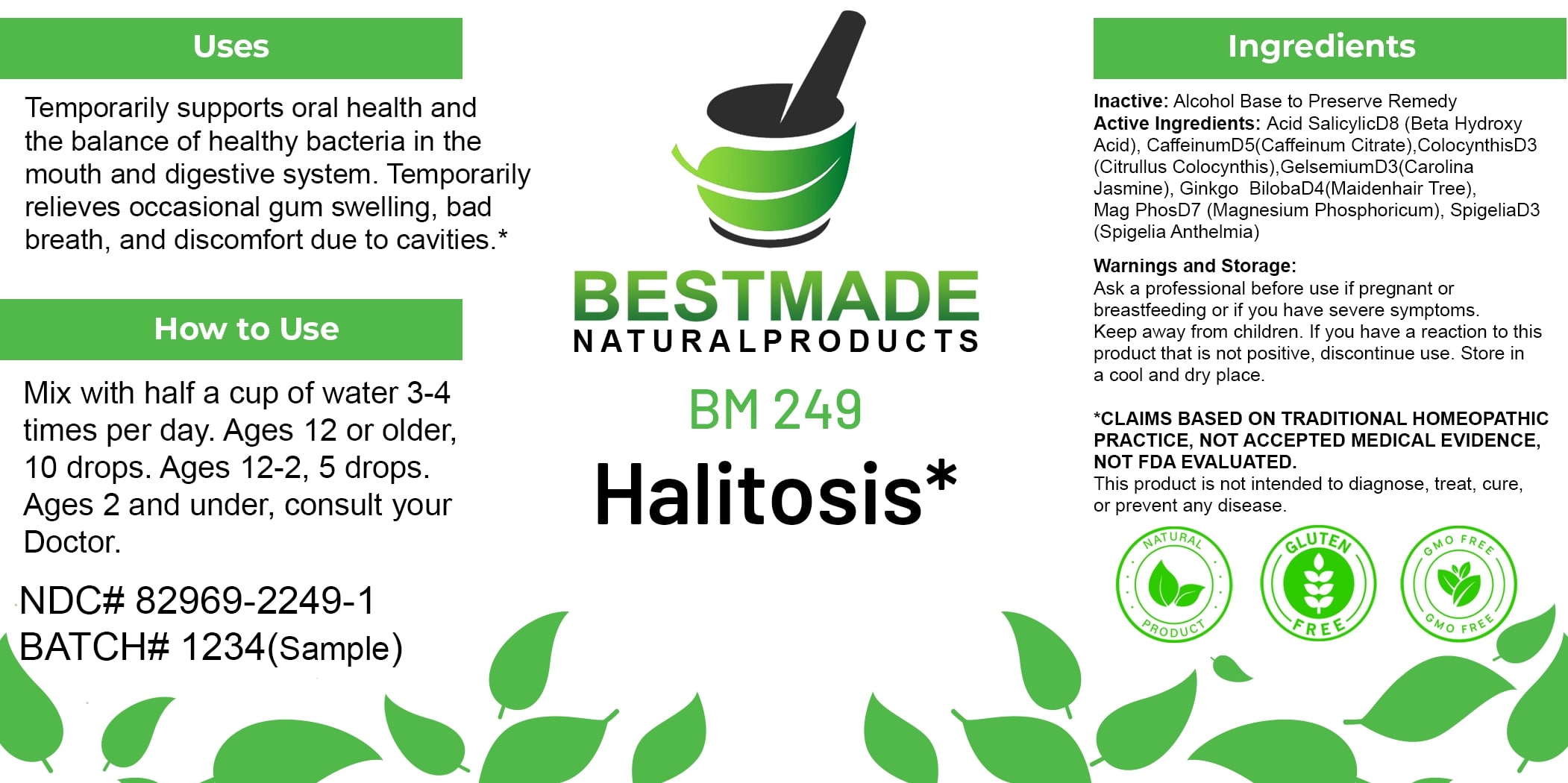 DRUG LABEL: Bestmade Natural Products BM249
NDC: 82969-2249 | Form: LIQUID
Manufacturer: Bestmade Natural Products
Category: homeopathic | Type: HUMAN OTC DRUG LABEL
Date: 20250305

ACTIVE INGREDIENTS: GINKGO 30 [hp_C]/30 [hp_C]; GELSEMIUM SEMPERVIRENS ROOT 30 [hp_C]/30 [hp_C]; CITRULLUS COLOCYNTHIS FRUIT PULP 30 [hp_C]/30 [hp_C]; SPIGELIA ANTHELMIA 30 [hp_C]/30 [hp_C]; SALICYLIC ACID 30 [hp_C]/30 [hp_C]; CAFFEINE 30 [hp_C]/30 [hp_C]; MAGNESIUM PHOSPHATE, DIBASIC TRIHYDRATE 30 [hp_C]/30 [hp_C]
INACTIVE INGREDIENTS: ALCOHOL 30 [hp_C]/30 [hp_C]

BM249

DOSAGE AND ADMINISTRATION

How to Use

Mix with half a cup of water 3-4 times per day. Ages 12 or older, 10 drops. Ages 12-2, 5 drops. Ages 2 and under, consult your Doctor.

Uses

Temporarily supports oral health and the balance of healthy bacteria in the mouth and digestive system. Temporarily relieves occasional gum swelling, bad breath, and discomfort due to cavities.*

*CLAIMS BASED ON TRADITIONAL HOMEOPATHIC PRACTICE, NOT ACCEPTED MEDICAL EVIDENCE, NOT FDA EVALUATED.

This product is not intended to diagnose, treat, cure, or prevent any disease.

INACTIVE INGREDIENT

Ingredients

Inactive: Alcohol Base to Preserve Remedy

ACTIVE INGREDIENT

Active Ingredients: Acid SalicylicD8 (Beta Hydroxy Acid), CaffeinumD5 (Caffeinum Citrate), ColocynthisD3 (Citrullus Colocynthis), GelsemiumD3 (Carolina Jasmine), Ginkgo BilobaD4 (Maidenhair Tree), Mag PhosD7 (Magnesium Phosphoricum), SpigeliaD3 (Spigelia Anthelmia)

KEEP OUT OF REACH OF CHILDREN

Warnings and Storage:

Ask a professional before use if pregnant or breastfeeding or if you have severe symptoms. Keep away from children. If you have a reaction to this product that is not positive, discontinue use. Store in a cool and dry place.

Warnings and Storage:

Ask a professional before use if pregnant or breastfeeding or if you have severe symptoms. Keep away from children. If you have a reaction to this product that is not positive, discontinue use. Store in a cool and dry place.

*CLAIMS BASED ON TRADITIONAL HOMEOPATHIC PRACTICE, NOT ACCEPTED MEDICAL EVIDENCE, NOT FDA EVALUATED.

This product is not intended to diagnose, treat, cure, or prevent any disease.

Uses

Temporarily supports oral health and the balance of healthy bacteria in the mouth and digestive system. Temporarily relieves occasional gum swelling, bad breath, and discomfort due to cavities.*

*CLAIMS BASED ON TRADITIONAL HOMEOPATHIC PRACTICE, NOT ACCEPTED MEDICAL EVIDENCE, NOT FDA EVALUATED.

This product is not intended to diagnose, treat, cure, or prevent any disease.

Entire package label